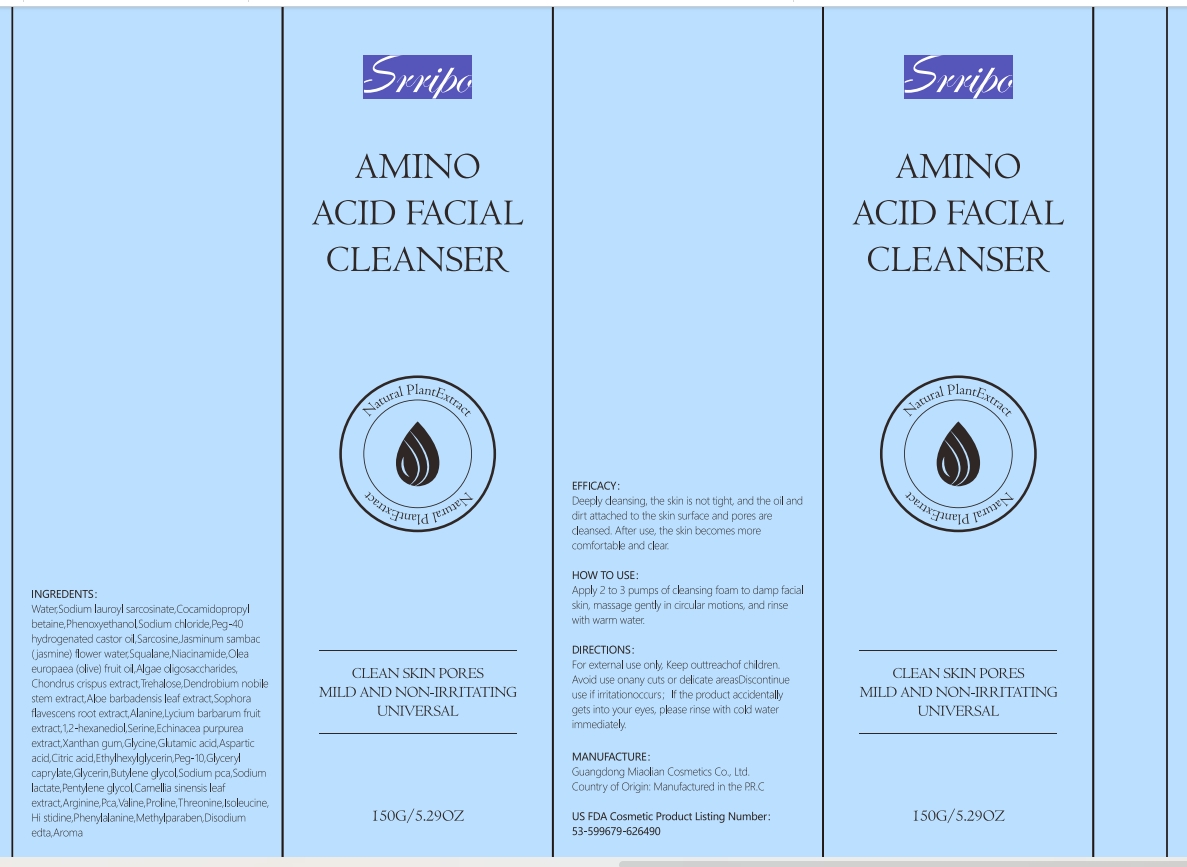 DRUG LABEL: Srripo Amino Acid Facial Cleanser
NDC: 84507-023 | Form: CREAM
Manufacturer: Guangdong Miaolian Cosmetics Co., Ltd.
Category: otc | Type: HUMAN OTC DRUG LABEL
Date: 20240923

ACTIVE INGREDIENTS: COCAMIDOPROPYL BETAINE 1.5 mg/100 g
INACTIVE INGREDIENTS: ARGININE; HISTIDINE; ASPARTIC ACID; TREHALOSE; SODIUM SULFATE; EDETATE DISODIUM; GLYCINE; SODIUM LACTATE; CAMELLIA SINENSIS FLOWER; PENTYLENE GLYCOL; SQUALANE; LYCIUM BARBARUM FRUIT; GLYCERYL CAPRYLATE; JASMINUM SAMBAC FLOWER; ALANINE; VALINE; OLEA EUROPAEA FRUIT VOLATILE OIL; WATER; THREONINE; DENDROBIUM NOBILE STEM; PROLINE; SODIUM CHLORIDE; GLUTAMIC ACID; ETHYLHEXYLGLYCERIN; POLYOXYL 40 HYDROGENATED CASTOR OIL; SERINE; ISOLEUCINE; PHENYLALANINE; ALOE; SARCOSINE; 1,2-HEXANEDIOL; SOPHORA FLAVESCENS ROOT; SODIUM LAUROYL SARCOSINATE; METHYLPARABEN; ECHINACEA PURPUREA; XANTHAN GUM; BUTYLENE GLYCOL; GLYCERIN; PHENOXYETHANOL

DOSAGE AND ADMINISTRATION

Take appropriate amount of this product on the palm, gently rub with water until it is rich in foam, apply it on the wet face, massage it easily,then rinse by clean water.

WARNINGS

For external use only
Ask a doctor before using. If you have a history of allergies to such products
When using this product avoid contact with the eyes.
if contact occurs, rinse eyes thoroughly with water.Stop use and ask a doctor if condition worsens
condition does not improve after regular use of this product as directed.
Keep outof reach of children.
If pregnant or breast-feeding, please use with care.

INACTIVE INGREDIENT

WATER
SODIUM CHLORIDE
SODIUM SULFATE
SARCOSINE
GLYCINE
GLUTAMIC ACID
ASPARTIC ACID
PHENOXYETHANOL
ETHYLHEXYLGLYCERIN
GLYCERYL CAPRYLATE
PEG-40 HYDROGENATED CASTOR OIL
PEG-10
JASMINUM SAMBAC (JASMINE) FLOWER WATER
METHYLPARABEN
AROMA
DISODIUM EDTA
CITRIC ACID
SODIUM PCA
SODIUM LACTATE
ARGININE
PCA
ALANINE
SERINE
VALINE
PROLINE
THREONINE
ISOLEUCINE
HISTIDINE
PHENYLALANINE
BUTYLENE GLYCOL
CAMELLIA SINENSIS LEAF EXTRACT
GLYCERIN
TREHALOSE
DENDROBIUM NOBILE STEM EXTRACT
ALOE BARBADENSIS LEAF EXTRACT
PENTYLENE GLYCOL
SOPHORA FLAVESCENS ROOT EXTRACT
LYCIUM BARBARUM FRUIT EXTRACT
1,2-HEXANEDIOL
ECHINACEA PURPUREA EXTRACT
XANTHAN GUM
OLEA EUROPAEA (OLIVE) FRUIT OIL
SQUALANE

INDICATIONS AND USAGE

Deeply cleansing, the skin is not tight, and the oil and dirt attached to the skin surface and pores are cleansed. After use, the skin becomes more comfortable and clear.

Keep out of reach of children.

PURPOSE

Deeply cleansing,After use, the skin becomes more comfortable and clear.

ACTIVE INGREDIENT

SODIUM LAUROYL SARCOSINATE
COCAMIDOPROPYL BETAINE